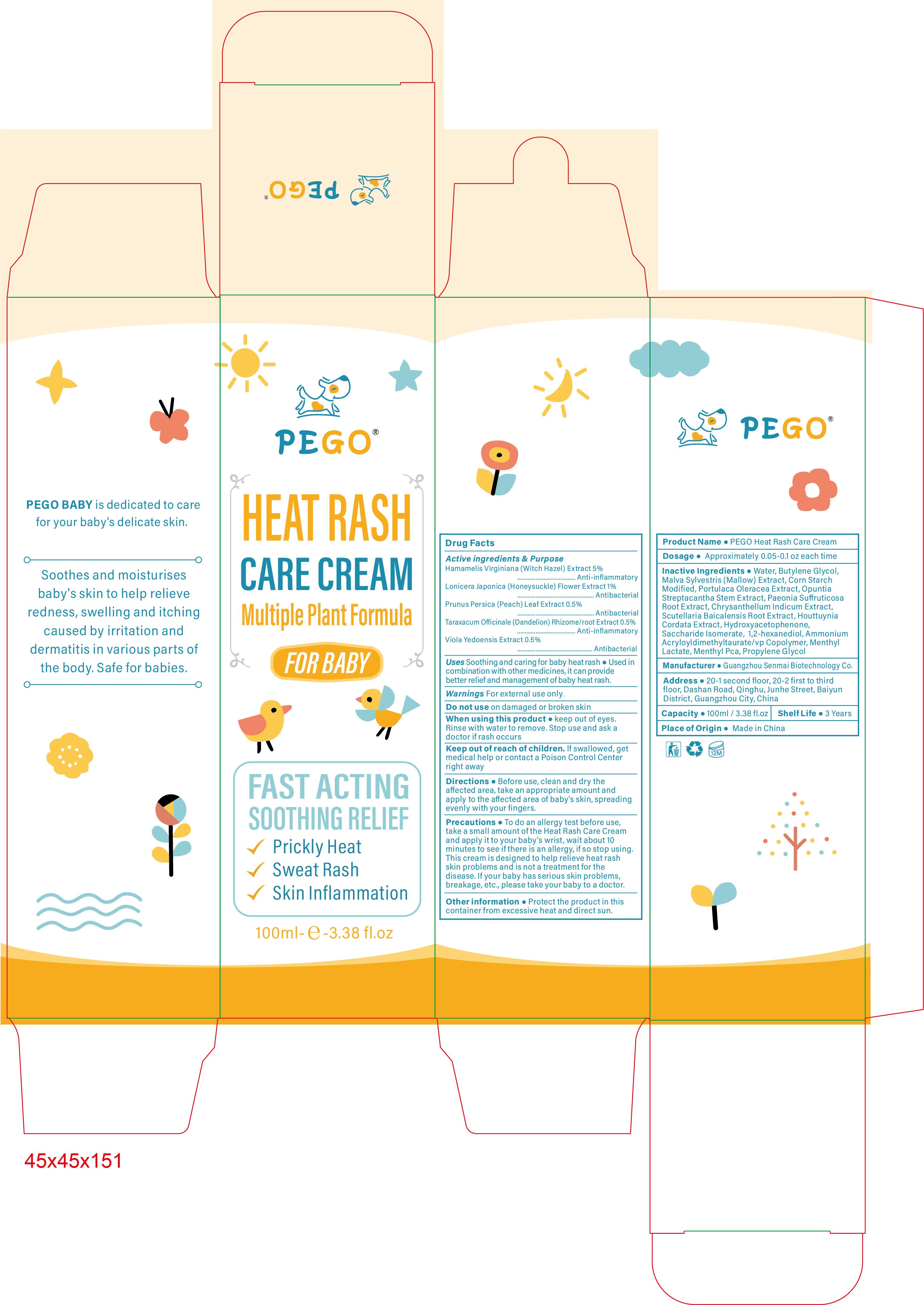 DRUG LABEL: PEGO Heat Rash Care Cream
NDC: 84509-013 | Form: CREAM
Manufacturer: Guangzhou Senmai Biotechnology Co.
Category: otc | Type: HUMAN OTC DRUG LABEL
Date: 20240909

ACTIVE INGREDIENTS: HAMAMELIS VIRGINIANA LEAF 5000 mg/100 mL; LONICERA JAPONICA FLOWER 1000 mg/100 mL; PRUNUS PERSICA LEAF 500 mg/100 mL; VIOLA PHILIPPICA WHOLE 500 mg/100 mL; TARAXACUM OFFICINALE ROOT 500 mg/100 mL
INACTIVE INGREDIENTS: WATER; SCUTELLARIA BAICALENSIS ROOT; METHYL LACTATE, (-)-; PROPYLENE GLYCOL; PURSLANE; AMMONIUM ACRYLOYLDIMETHYLTAURATE/VP COPOLYMER; MENTHYL DL-PYRROLIDONECARBOXYLATE; STARCH, CORN; 1,2-HEXANEDIOL; OPUNTIA STREPTACANTHA STEM; CHRYSANTHELLUM INDICUM TOP; HOUTTUYNIA CORDATA FLOWERING TOP; HYDROXYACETOPHENONE; MALVA SYLVESTRIS FLOWERING TOP; PAEONIA SUFFRUTICOSA ROOT; BUTYLENE GLYCOL; SACCHARIDE ISOMERATE

Active Ingredients

Hamamelis Virginiana (Witch Hazel) Extract 5%
Lonicera Japonica (Honeysuckle) Flower Extract 1%
Prunus Persica (Peach) Leaf Extract 0.5%
Taraxacum Officinale (Dandelion) Rhizome/root Extract 0.5%

Viola Yedoensis Extract 0.5%

Purpose

Anti-inflammatory

Antibacterial

Uses

Soothing and caring for baby heat rash , Used in combination with other medicines, it can provide better relief and management of baby heat rash.

Warnings

For external use only.

Do not use

on damaged or broken skin.

When using this product

Keep out of eyes. Rinse with water to remove. Stop use and ask a doctor if rash occurs.

Keep out of reach of children.

If swallowed, get medical help or contact a Poison Control Center right away

Directions

Before use, clean and dry the affected area,take an appropriate amount and apply to the affected area of baby's skin,spreading evenly with your fingers.

Precautions

To do an allergy test before use,take a small amount of the Heat Rash Care Cream and apply it to your baby's wrist, wait about 10 minutes to see if there is an allergy, if so stop using.This cream is designed to help relieve heat rash skin problems and is not a treatment for the disease.lf your baby has serious skin problems,breakage,etc., please take your baby to a doctor.

Other information

Protect the product in this container from excessive heat and direct sun.

Product Name

PEGO Heat Rash Care Cream

Dosagee

Approximately 0.05-01 oz each time

Inactive Ingredients

Water, Butylene Glycol,Malva Sylvestris(Mallow) Extract, Corn Starch Modified,Portulaca Oleracea Extract,Opuntia Streptacantha Stem Extract,Paeonia Suffruticosa Root Extract,Chrysanthellum Indicum Extract,Scutellaria Baicalensis Root Extract, Houttuynia Cordata Extract,Hydroxyacetophenone,Saccharide lsomerate,1.2-hexanediol,Ammonium Acryloyldimethyltaurate/vp Copolymer, Menthyl Lactate,Menthyl Pca, Propylene Glycol

Manufacturer

Guangzhou Senmai Biotechnology Co.

Address

20-1second floor, 20-2 first to third floor,Dashan Road,Qinghu,Junhe Street, Baiyun district, Guangzhou City, China.

Capacity

100ml-e-3.38 fl.oz

Shelf Life

3 Years

Place of Origin

Made in China